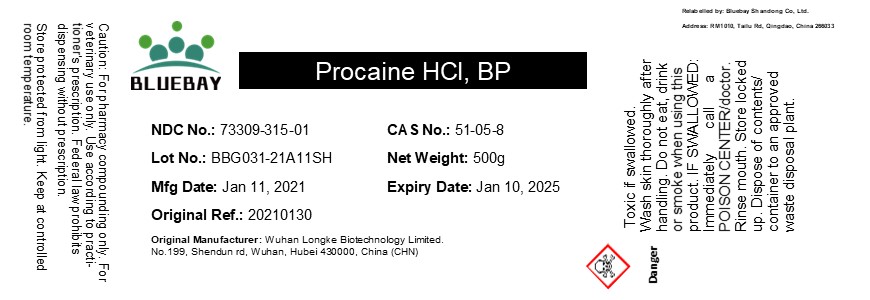 DRUG LABEL: Procaine HCl
NDC: 73309-315 | Form: POWDER
Manufacturer: BLUEBAY SHANDONG CO.,LTD
Category: other | Type: BULK INGREDIENT
Date: 20210803

ACTIVE INGREDIENTS: PROCAINE HYDROCHLORIDE 1 g/1 g

Procaine HCl